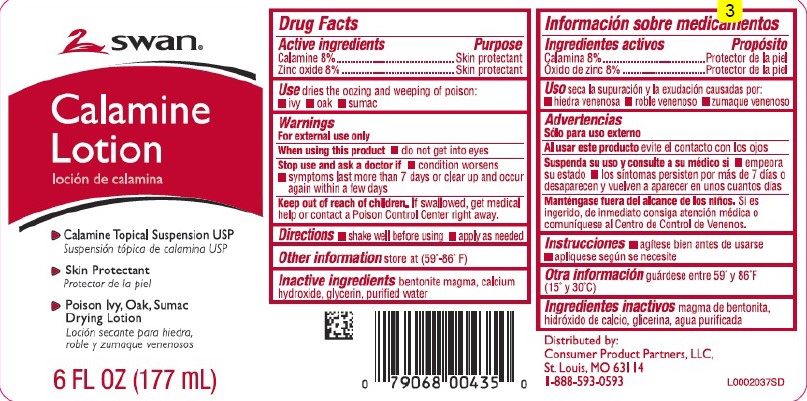 DRUG LABEL: Calamine
NDC: 11344-063 | Form: LOTION
Manufacturer: Consumer Product Partners, LLC
Category: otc | Type: HUMAN OTC DRUG LABEL
Date: 20250306

ACTIVE INGREDIENTS: FERRIC OXIDE RED 80 mg/1 mL; ZINC OXIDE 80 mg/1 mL
INACTIVE INGREDIENTS: BENTONITE; CALCIUM HYDROXIDE; GLYCERIN; WATER

Swan 063.001/063AA
Calamine Lotion

Active ingredients

Calamine 8%

Zinc oxide 8%

Purpose

Skin protectant

Use

dries the oozing and weeping of poison:•i vy • oak • sumac

Warnings

For external use only

When using this product

Do not get into eyes

Stop use and ask a doctor if

- condition worsens
- symptoms last more than 7 days or clear up and occur again within a few days

Keep out of reach of children

If swallowed, get medical help or contact a Poison Control Center right away.

Directions

- shake well before using
- apply as needed

Other information

store at 59⁰ - 86⁰F

Inactive ingredients

bentonite magma, calcium hydroxide, glycerin, purified water

Adverse reaction

Distributed by:

Consumer Product Partners, LLC,

St. Louis, MO 63114

1-888-593-0593

Principal Panel Display

SWAN®

Calamine Lotion

- Calamine topical Suspension USP
- Skin Protectant
- Poison Ivy, Oak, Sumac Drying Lotion

6 FL OZ (177 mL)